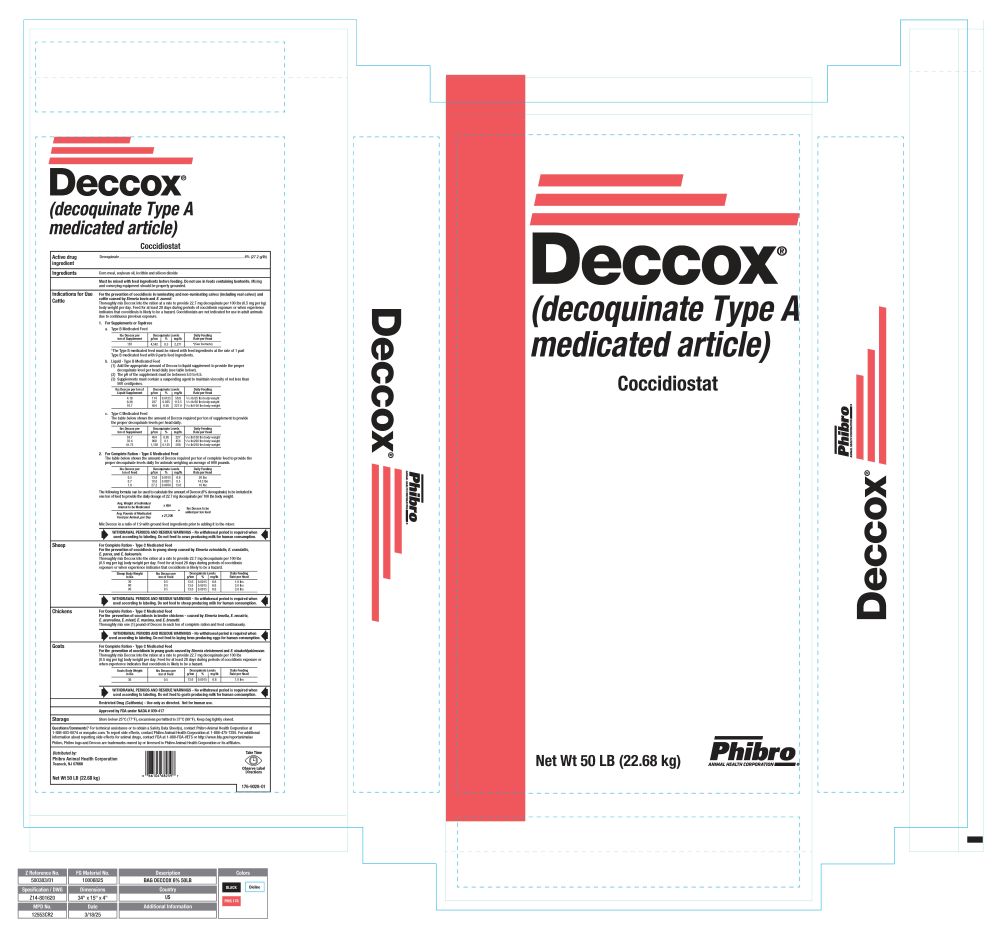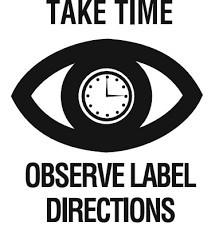 DRUG LABEL: Deccox
NDC: 66104-6825 | Form: GRANULE
Manufacturer: Phibro Animal Health
Category: animal | Type: OTC TYPE A MEDICATED ARTICLE ANIMAL DRUG LABEL
Date: 20260224

ACTIVE INGREDIENTS: DECOQUINATE 27.2 g/0.45 kg

Deccox®

Deccox

(Decoquinate Type A Medicated Article)
Coccidiostat

Active ingredient

Decoquinate................................................................................................................. 6% (27.2 g/lb)

Ingredients

Corn meal, soybean oil, lecithin and silicon dioxide

DOSAGE AND ADMINISTRATION

Must be mixed with feed ingredients before feeding. Do not use in feeds containing bentonite. Mixing and conveying equipment should be properly grounded.

Cattle

DOSAGE AND ADMINISTRATION

Indications for Use:

For the prevention of coccidiosis in ruminating and non-ruminating calves (including veal calves) and cattle caused by Eimeria bovis and E. zuernii.

Thoroughly mix Deccox into the ration at a rate to provide 22.7 mg decoquinate per 100lbs (0.5 mg per kg) of body weight per day. Feed for at least 28 days during periods of coccidiosis exposure or when experience indicates that coccidiosis is likely to be a hazard. Coccidiostats are not indicated for use in adult animals due to continuous previous exposure.

- 1. For Supplements or Topdress

- a. Type B Medicated Feed

lbs Deccox per ton of Supplement | Decoquinate Levels |  |  | Daily Feeding Rate per Head
lbs Deccox per ton of Supplement | g/ton | % | mg/lb | Daily Feeding Rate per Head
167 | 4,542 | 0.5 | 2271 | *(See footnote)

*The Type B medicated feed must be mixed with feed ingredients at the rate of 1 part Type B medicated feed with 9 parts feed ingredients.

b. Liquid - Type B Medicated Feed

(1)Add the appropriate amount of Deccox to liquid supplement to provide the proper decoquinate level per head daily (see table below).
(2)The pH of the supplement must be between 5.0 to 6.5.
(3)Supplements must contain a suspending agent to maintain viscosity of not less than 500 centipoises.

lbs Deccox per ton of Liquid Supplement | Decoquinate Levels |  |  | Daily Feeding Rate per Head
lbs Deccox per ton of Liquid Supplement | g/ton | % | mg/lb | Daily Feeding Rate per Head
4.18 | 114 | 0.0125 | 56.8 | ^1/10 lb/25 lbs body weight
8.36 | 227 | 0.025 | 113.5 | ^1/10 lb/50 lbs body weight
16.7 | 454 | 0.05 | 227.0 | ^1/10 lb/100 lbs body weight

c .Type C Medicated Feed

The table below shows the amount of Deccox required per ton of supplement to provide proper decoquinate levels per head daily

lbs Deccox per ton of Feed | Decoquinate Levels |  |  | Daily Feeding Rate per Head
lbs Deccox per ton of Feed | g/ton | % | mg/lb | Daily Feeding Rate per Head
16.7 | 454 | 0.05 | 227 | 1/10 lb/100 lbs body weight
33.4 | 908 | 0.1 | 454 | 1/10 lb/200 lbs body weight
41.75 | 1,136 | 0.125 | 568 | 1/10 lb/250 lbs body weight

2. For Complete Ration - Type C Medicated Feed

The table below shows the amount of Deccox required per ton of complete feed to provide proper decoquinate levels daily for animals weighing an average of 600 pounds.

lbs Deccox per ton of Feed | Decoquinate Levels |  |  | Daily FeedingRate per Head
 | g/ton | % | mg/lb
0.5 | 13.6 | 0.0015 | 6.8 | 20 lbs
0.7 | 19.0 | 0.0021 | 9.5 | 14.3 lbs
1.0 | 27.2 | 0.0030 | 13.6 | 10 lbs

The following formula can be used to calculate the amount of Deccox (6% decoquinate) to be included in one ton of feed to provide the daily dosage of 22.7 mg decoquinate per 100 lbs body weight.

Avg. Weight of Individual Animal to be Medicated | × 454 | = | lbs Deccox to be added per ton feed
Avg. Pounds of Medicated Feed per Animal, per Day | × 27,200 | = | lbs Deccox to be added per ton feed

Mix Deccox in a ratio of 1:9 with ground feed ingredients prior to adding it to the mixer.

WITHDRAWAL PERIODS AND RESIDUE WARNINGS

No withdrawal period is required when used according to labeling. Do not feed to cows producing milk for human consumption

Sheep

DOSAGE AND ADMINISTRATION

For Complete Ration - Type C Medicated Feed

For the prevention of coccidiosis in young sheep caused by Eimeria ovinoidalis, E. crandallis, E. parva, and E. bakuensis.

Thoroughly mix Deccox into the ration at a rate to provide 22.7 mg decoquinate per 100 lbs (0.5 mg per kg) of body weight per day. Feed for at least 28 days during periods of coccidiosis exposure or when experience indicates that coccidiosis is likely to be a hazard.

Sheep Body Weight in lbs | lbs Deccox per ton of Feed | Decoquinate Levels |  |  | Daily Feeding Rate per Head
Sheep Body Weight in lbs | lbs Deccox per ton of Feed | g/ton | % | mg/lb | Daily Feeding Rate per Head
30 | 0.5 | 13.6 | 0.0015 | 6.8 | 1.0 lbs
60 | 0.5 | 13.6 | 0.0015 | 6.8 | 2.0 lbs
90 | 0.5 | 13.6 | 0.0015 | 6.8 | 3.0 lbs

WITHDRAWAL PERIODS AND RESIDUE WARNINGS

No withdrawal period is required when used according to labeling. Do not feed to sheep producing milk for human consumption

Chickens

DOSAGE AND ADMINISTRATION

For Complete Ration - Type C Medicated Feed

For the prevention of coccidiosis in broiler chickens - caused by Eimeria tenella, E. necatrix, E. acervulina, E. mivati, E. maxima, and E. brunetti.

Thoroughly mix one (1) pound of Deccox in each ton of complete ration and feed continuously

WITHDRAWAL PERIODS AND RESIDUE WARNINGS

No withdrawal period is required when used according to labeling. Do not feed to laying hens producing eggs for human consumption

Goats

DOSAGE AND ADMINISTRATION

For Complete Ration - Type C Medicated Feed

For the prevention of coccidiosis in young goats caused by Eimeria christenseni and E. ninakohlyakimovae.

Thoroughly mix Deccox into the ration at a rate to provide 22.7 mg decoquinate per 100 lbs (0.5 mg per kg) of body weight per day. Feed for at least 28 days during periods of coccidiosis exposure or when experience indicates that coccidiosis is likely to be a hazard.

Goats Body Weight in lbs | lbs Deccox per ton of Feed | Decoquinate Levels |  |  | Daily Feeding Rate per Head
Goats Body Weight in lbs | lbs Deccox per ton of Feed | g/ton | % | mg/lb | Daily Feeding Rate per Head
30 | 0.5 | 13.6 | 0.0015 | 6.8 | 1.0 lbs

WITHDRAWAL PERIOD AND RESIDUE WARNINGS

No withdrawal period is required when used according to labeling. Do not feed to goats producing milk for human consumption

Restricted Drug (California) - Use only as directed. Not for human use.

Approved by FDA under NADA # 039-417

Storage

Store below 25°C (77°F), excursions permitted to 37°C (99°F). Keep bag tightly closed.

Questions/Comments? For technical assistance or to obtain a Safety Data Sheet(s), contact Phibro Animal
Health at 888-403-0074 or www.pahc.com. To report side effects, contact Phibro Animal Health Corporation at
1-888-475-7355. For additional information about reporting side effects for animal drugs, contact FDA at
1-888-FDA-VETS or http://www.fda.gov/reportanimalae

Phibro, Phibro logo and BMD are trademarks owned by or licensed to Phibro Animal Health Corporation or its affiliates.

Distributed by:
Phibro Animal Health Corporation
Teaneck, NJ 07666

Net Wt 50 LB (22.68 kg)
176-9016-02

Deccox

Deccox Label